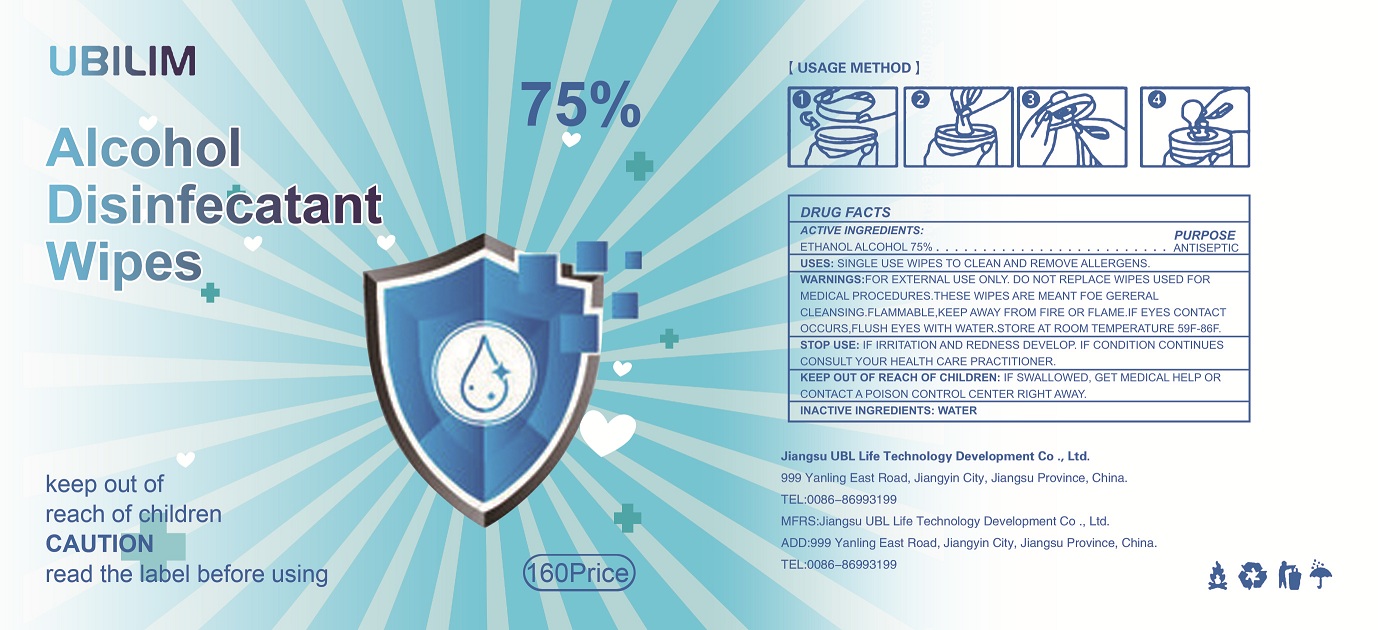 DRUG LABEL: UBLIM Alcohol Disinfectant
NDC: 81395-001 | Form: CLOTH
Manufacturer: Jiangsu UBL Life Technology Development Co., Ltd.
Category: otc | Type: HUMAN OTC DRUG LABEL
Date: 20210312

ACTIVE INGREDIENTS: ALCOHOL 75 1/100 1
INACTIVE INGREDIENTS: WATER

DOSAGE AND ADMINISTRATION

Single use wipes to clean and remove all allergens.

INACTIVE INGREDIENT

Water

ACTIVE INGREDIENT

Ethanol Alcohol: 75%…………………Antiseptic

KEEP OUT OF REACH OF CHILDREN

If swallowed, get medical help or contact a poison control center right away.

Stop use if irrication and redness develop. If condition continues consult your health care practitioner.

WARNINGS

For external use only.

Do not replace wipes used for medical procedures. These wipes are meant for general cleasing.

Flammable, keep away from fire or flame.

If eye contact occurs, flush eyes with water.

Store at room temperature 59F-86F.

PURPOSE

These wipes are meant for general cleasing.

INDICATIONS AND USAGE

Single use wipes to clean and remove allergebs.